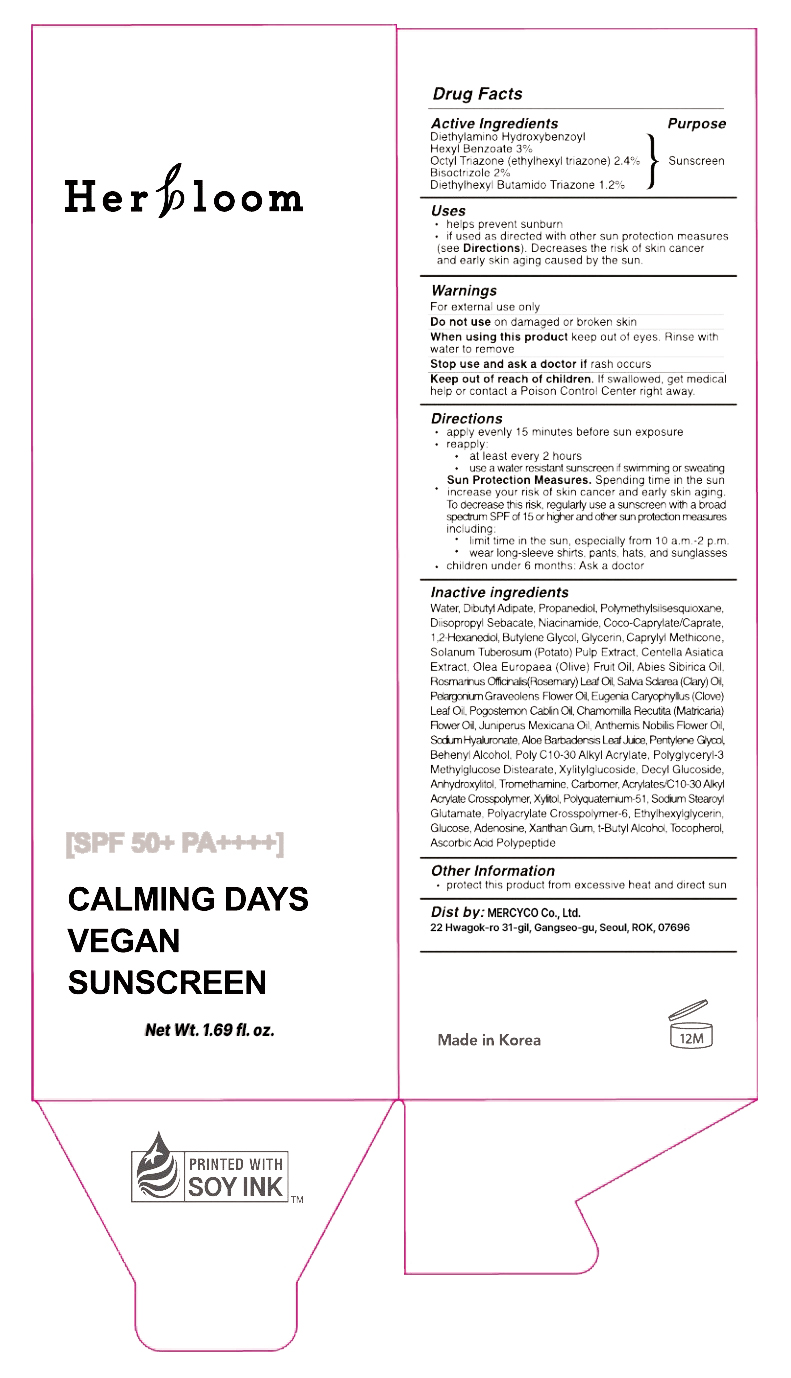 DRUG LABEL: Calming Days Vegan Sunscreen
NDC: 85940-307 | Form: GEL
Manufacturer: MERCYCO Co., Ltd.
Category: otc | Type: HUMAN OTC DRUG LABEL
Date: 20251229

ACTIVE INGREDIENTS: DIETHYLAMINO HYDROXYBENZOYL HEXYL BENZOATE 3 g/100 mL; BISOCTRIZOLE 2 g/100 mL; ISCOTRIZINOL 1.2 g/100 mL; ETHYLHEXYL TRIAZONE 2.4 g/100 mL
INACTIVE INGREDIENTS: ANHYDROUS DEXTROSE; WATER; XANTHAN GUM; TOCOPHEROL; PELARGONIUM GRAVEOLENS FLOWER OIL; COCO-CAPRYLATE/CAPRATE; XYLITYLGLUCOSIDE; BUTYLENE GLYCOL PROPIONATE; POLYQUATERNIUM-51 (2-METHACRYLOYLOXYETHYL PHOSPHORYLCHOLINE/N-BUTYL METHACRYLATE; 3:7); CAPRYLYL TRISILOXANE; DOCOSANOL; OLIVE OIL; ROSEMARY OIL; CHAMOMILE FLOWER OIL; ACRYLATES CROSSPOLYMER-4; SODIUM STEAROYL GLUTAMATE; AMMONIUM ACRYLOYLDIMETHYLTAURATE, DIMETHYLACRYLAMIDE, LAURYL METHACRYLATE AND LAURETH-4 METHACRYLATE COPOLYMER, TRIMETHYLOLPROPANE TRIACRYLATE CROSSLINKED (45000 MPA.S); TROMETHAMINE; ASCORBIC ACID; ADENOSINE; CENTELLA ASIATICA TRITERPENOIDS; JUNIPERUS DEPPEANA WOOD OIL; DIISOPROPYL SEBACATE; CARBOMER HOMOPOLYMER, UNSPECIFIED TYPE; ANHYDROXYLITOL; PENTYLENE GLYCOL; CLARY SAGE OIL; ETHYLHEXYLGLYCERIN; DIBUTYL ADIPATE; ABIES SIBIRICA LEAF OIL; POTATO PULP; CHAMAEMELUM NOBILE FLOWER OIL; BEHENYL ACRYLATE POLYMER; DECYL GLUCOSIDE; ALOE VERA LEAF; GLYCERIN; POGOSTEMON CABLIN LEAF OIL; XYLITOL; POLYMETHYLSILSESQUIOXANE (4.5 MICRONS); 1,2-HEXANEDIOL; PROPANEDIOL; POLYGLYCERYL-3 METHYLGLUCOSE DISTEARATE; NIACINAMIDE; CLOVE LEAF OIL; PEG-9 DIGLYCIDYL ETHER/SODIUM HYALURONATE CROSSPOLYMER; TERT-BUTYL ALCOHOL

85940-307

ACTIVE INGREDIENT

Diethylhexyl Butamido Triazone 1.2%

Bisoctrizole 2%

Octyl Triazone (ethylhexyl triazone) 2.4%

Diethylamino Hydroxybenzoyl Hexyl Benzoate 3%

PURPOSE

Sunscreen

INDICATIONS AND USAGE

• helps prevent sunburn

• if used as directed with other sun protection measures (see Directions). Decreases the risk of skin cancer and early skin aging caused by the sun.

WARNINGS

For external use only

When using this product keep out of eyes. Rinse with water to remove

Stop use and ask a doctor if rash occurs

Keep out of reach of children. If swallowed, get medical help or contact a Poison Control Center right away.

Keep out of reach of children. If swallowed, get medical help or contact a Poison Control Center right away.

Do not use on damaged or broken skin

DOSAGE AND ADMINISTRATION

• apply evenly 15 minutes before sun exposure

• reapply:

• at least every 2 hours

• use a water resistant sunscreen if swimming or sweating

• Sun Protection Measures. Spending time in the sun increase your risk of skin cancer and early skin aging.

To decrease this risk, regularly use a sunscreen with a broad spectrum SPF of 15 or higher and other sun protection measures

including:

• limit time in the sun, especially from 10 a.m.-2 p.m.

• wear long-sleeve shirts, pants, hats, and sunglasses

• children under 6 months: Ask a doctor

INACTIVE INGREDIENT

Water, Dibutyl Adipate, Propanediol, Polymethylsilsesquioxane,

Diisopropyl Sebacate, Coco-Caprylate/Caprate, 1,2-Hexanediol,

Butylene Glycol, Glycerin, Caprylyl Methicone, Solanum

Tuberosum (Potato) Pulp Extract, Centella Asiatica Extract,

Olea Europaea (Olive) Fruit Oil, Abies Sibirica Oil, Rosmarinus

Officinalis (Rosemary) Leaf Oil, Salvia Sclarea (Clary) Oil, Pelargonium

Graveolens Flower Oil, Eugenia Caryophyllus (Clove) Leaf Oil,

Pogostemon Cablin Oil, Chamomilla Recutita (Matricaria) Flower

Oil, Juniperus Mexicana Oil, Anthemis Nobilis Flower Oil,

Sodium Hyaluronate, Aloe Barbadensis Leaf Juice, Pentylene

Glycol, Behenyl Alcohol, Poly C10-30 Alkyl Acrylate, Polyglyceryl-3

Methylglucose Distearate, Xylitylglucoside, Decyl Glucoside,

Anhydroxylitol, Tromethamine, Carbomer, Acrylates/C10-30 Alkyl

Acrylate Crosspolymer, Xylitol, Polyquaternium-51, Sodium Stearoyl

Glutamate, Polyacrylate Crosspolymer-6, Ethylhexylglycerin,

Glucose, Xanthan Gum, T-Butyl Alcohol, Tocopherol, Ascorbic Acid

Polypeptide

85940

sunscreen